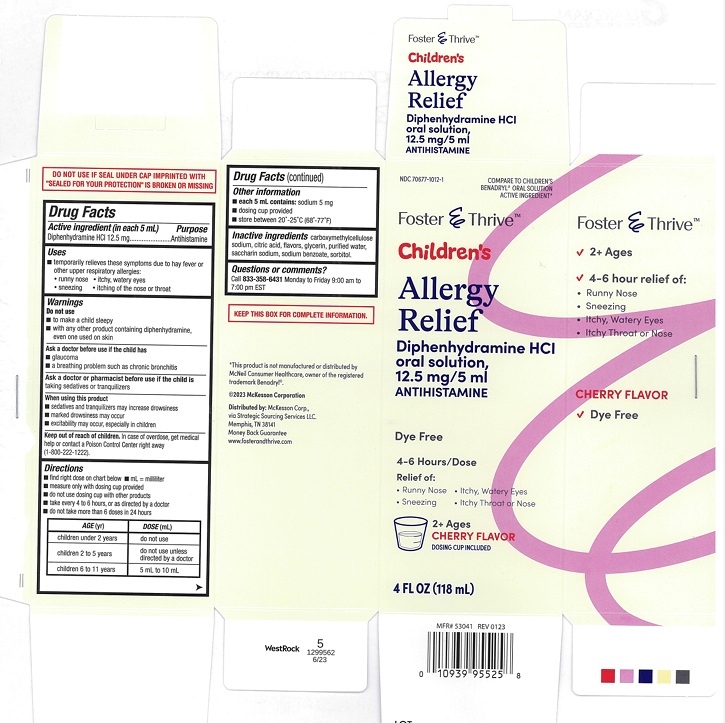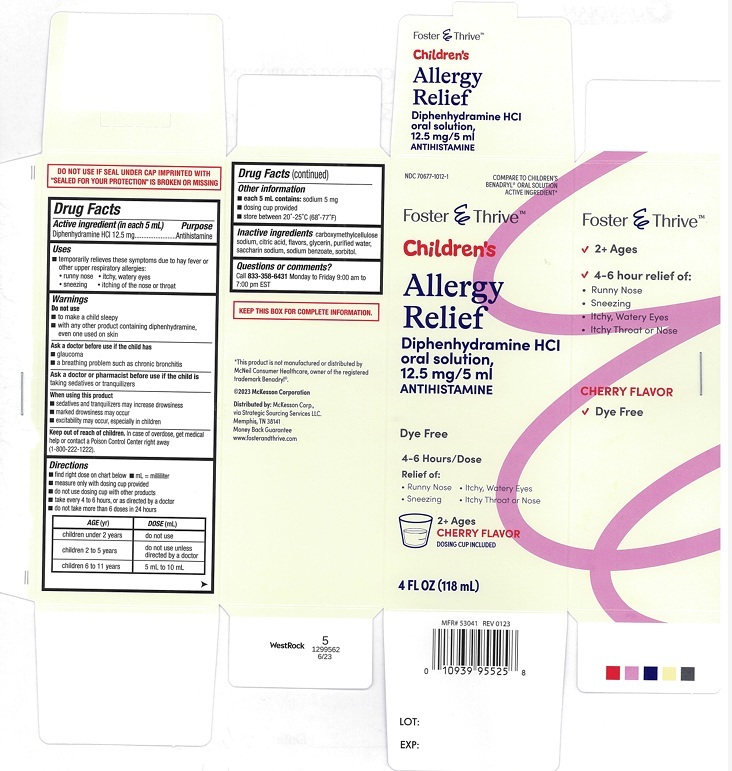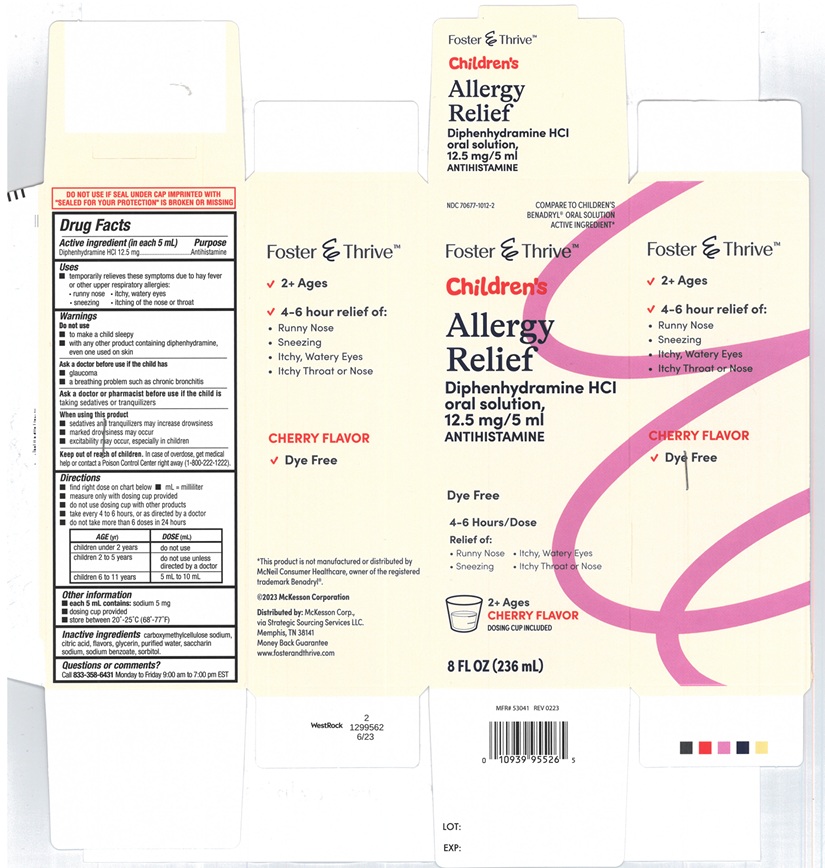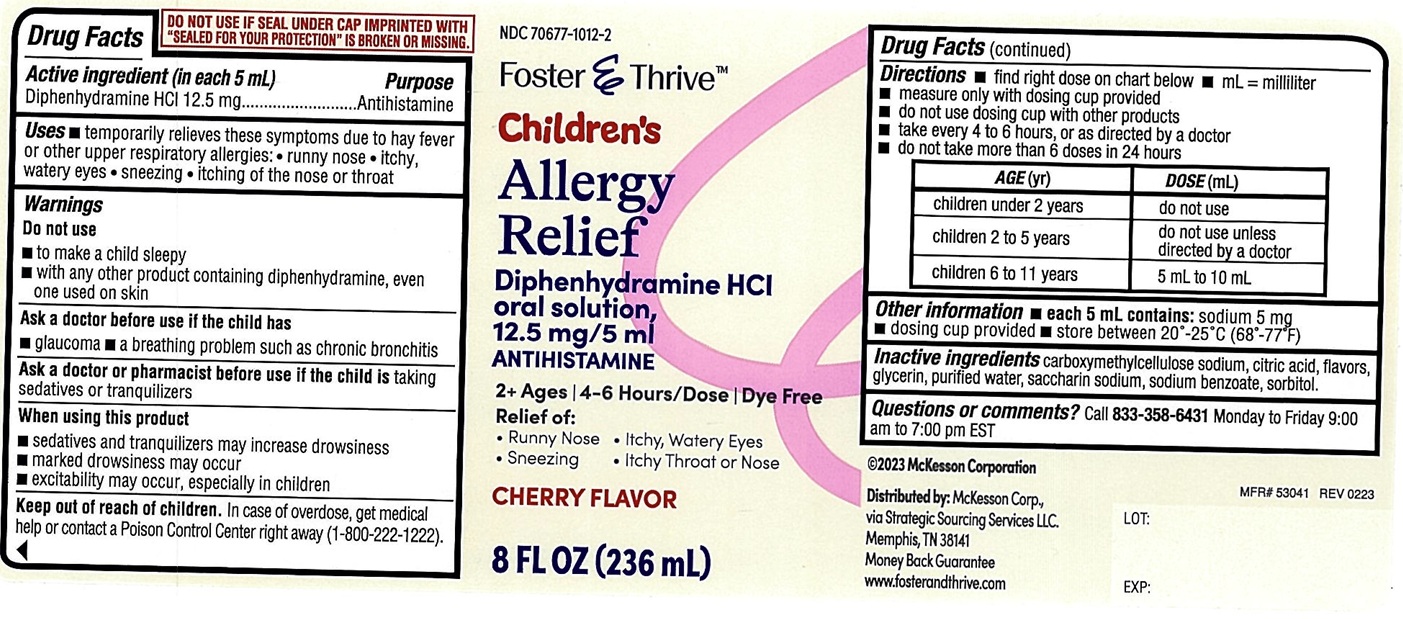 DRUG LABEL: Foster and Thrive Childrens Allergy Relief
NDC: 70677-1012 | Form: LIQUID
Manufacturer: Strategic Sourcing Services LLC
Category: otc | Type: Human OTC Drug Label
Date: 20241213

ACTIVE INGREDIENTS: DIPHENHYDRAMINE HYDROCHLORIDE 12.5 mg/5 mL
INACTIVE INGREDIENTS: CARBOXYMETHYLCELLULOSE SODIUM; ANHYDROUS CITRIC ACID; GLYCERIN; SACCHARIN SODIUM; WATER; SODIUM BENZOATE; SORBITOL

Foster and thrive childrens Allergy Relief 549

ACTIVE INGREDIENT(S)

Diphenhydramine HCl 12.5 mg

PURPOSE

Antihistamine

USE(S)

temporarily relieves these symptoms due to hay fever or other upper respiratory allergies:

- runny nose
- itchy, watery eyes
- sneezing
- itching of the nose or throat

WARNINGS

.

DO NOT USE

- to make a child sleepy
- with any other product containing diphenhydramine, even one used on skin

ASK A DOCTOR BEFORE USE IF THE CHILD HAS

- glaucoma
- a breathing problem such as chronic bronchitis

ASK A DOCTOR OR PHARMACIST BEFORE USE IF THE CHILD IS

taking sedatives or tranquilizers

WHEN USING THIS PRODUCT

- sedatives and tranquilizers may increase drowsiness
- marked drowsiness may occur
- excitability may occur, especially in children

KEEP OUT OF REACH OF CHILDREN.

In case of overdose, get medical help or contact a Poison Control Center right away (1-800-222-1222).

DIRECTIONS

- find right dose on chart below
- mL=milliliter
- measure only with dosing cup provided
- do not use dosing cup with other products
- take every 4 to 6 hours, or as directed by a doctor
- do not take more than 6 doses in 24 hours

AGE(yr) | DOSE(mL)
children under 2 years | do not use
children 2 to 5 years | do not use unless directed by a doctor
children 6 to 11 years | 5 mL to 10 mL

OTHER INFORMATION

- each 5 mL contains: sodium 5 mg
- dosing cup provided
- store between 20°-25°C(68°-77°F)

INACTIVE INGREDIENTS

carboxymethylcellulose sodium, citric acid, flavors, glycerin, purified water , saccharin sodium, sodium benzoate, sorbitol.

QUESTIONS OR COMMENTS

Call 833-358-6431 Monday to Friday 9:00 am to 7:00 pm EST

PRINCIPAL DISPLAY PANEL

NDC 70677-1012-2

COMPARE TO CHILDREN'S BENADRYL® ORAL SOLUTION ACTIVE INGREDIENT*

Foster & Thrive TM

Children's Allergy Relief

Diphenhydramine HCl oral solution,

12.5 mg/5ml

ANTIHISTAMINE

Dye Free

4-6 Hours/Dose

Relief of:

- Runny Nose
- Itchy Watery Eyes
- Sneezing
- Itchy Throat or Nose

2+ Ages

CHERRY FLAVOR

DOSING CUP INCLUDED

8FL OZ(236 mL)

NDC 70677-1012-1

COMPARE TO CHILDREN'S BENADRYL® ORAL SOLUTION ACTIVE INGREDIENT*

Foster & Thrive TM

Children's Allergy Relief

Diphenhydramine HCl oral solution,

12.5 mg/5ml

ANTIHISTAMINE

Dye Free

4-6 Hours/Dose

Relief of:

- Runny Nose
- Itchy Watery Eyes
- Sneezing
- Itchy Throat or Nose

2+Ages

CHERRY FLAVOR

DOSING CUP INCLUDED

4FL OZ(118 mL)